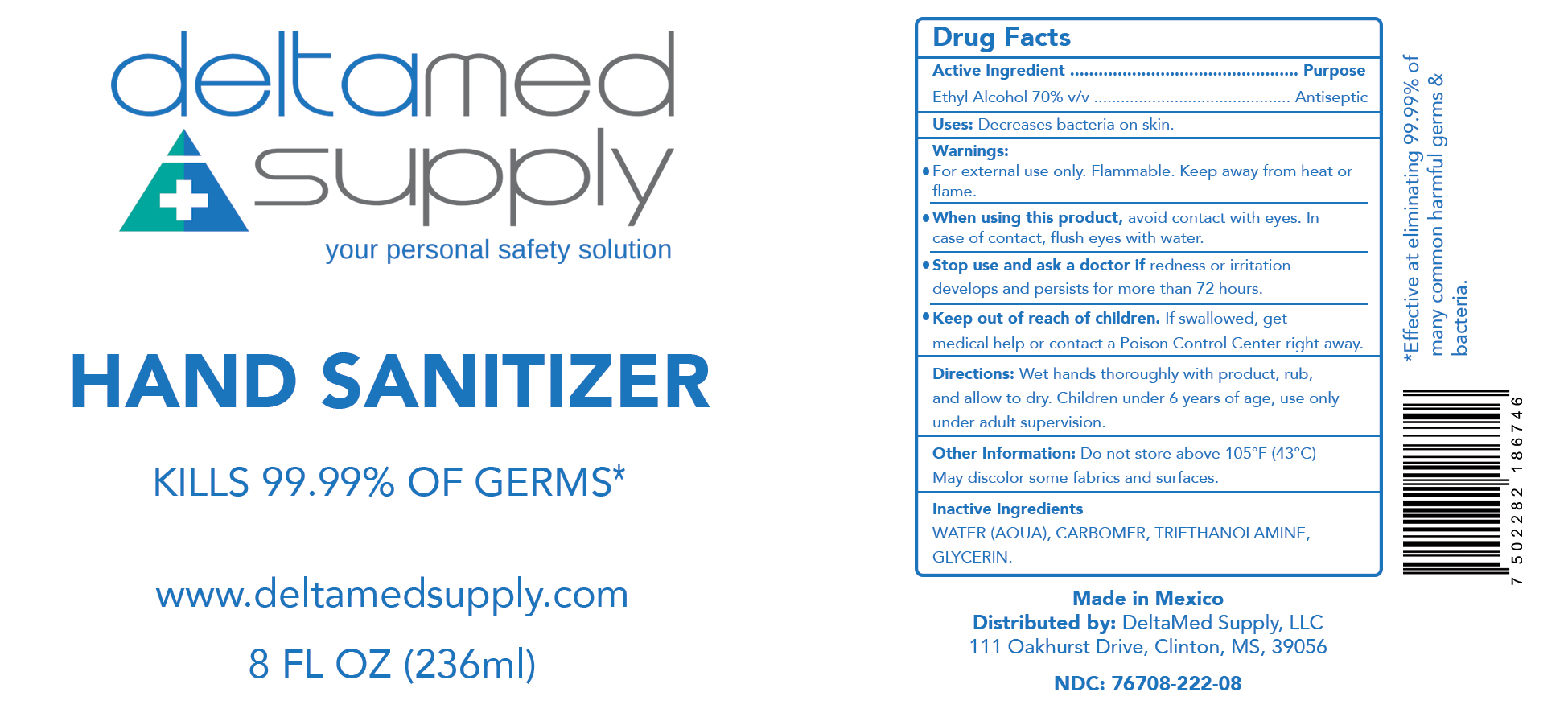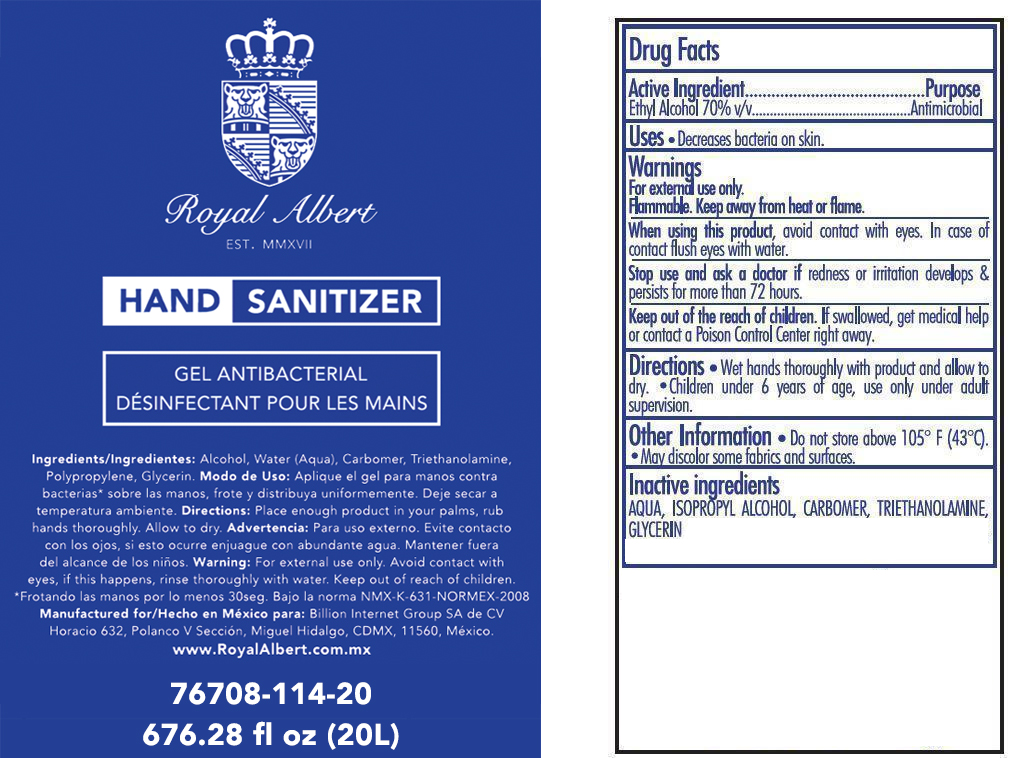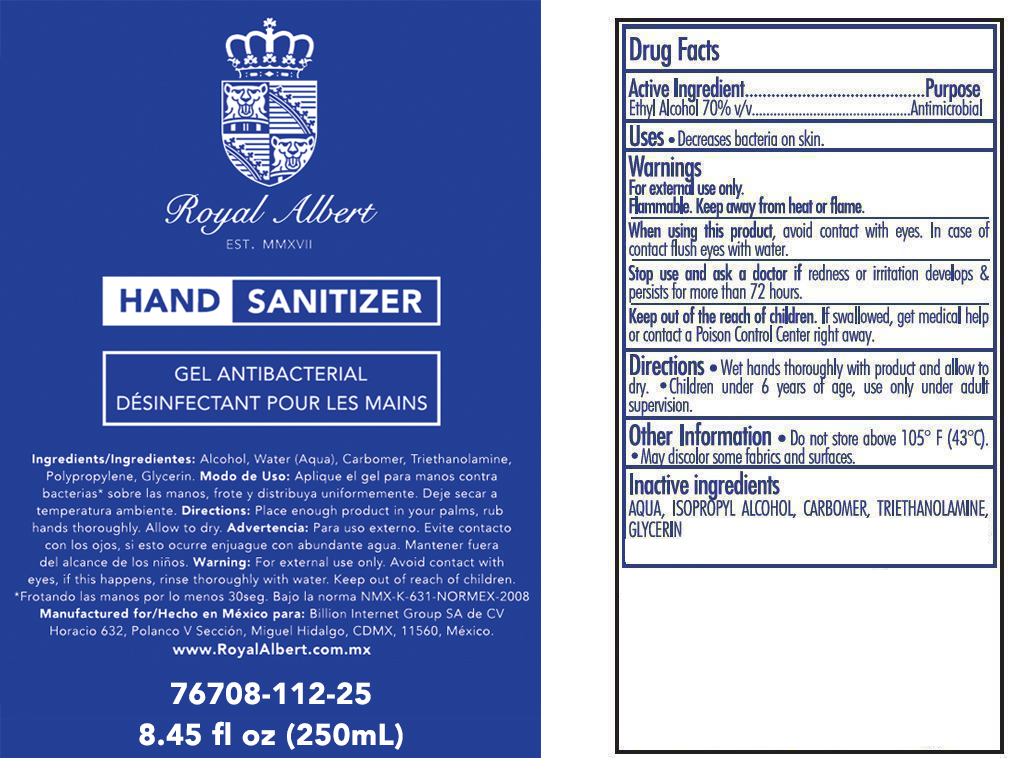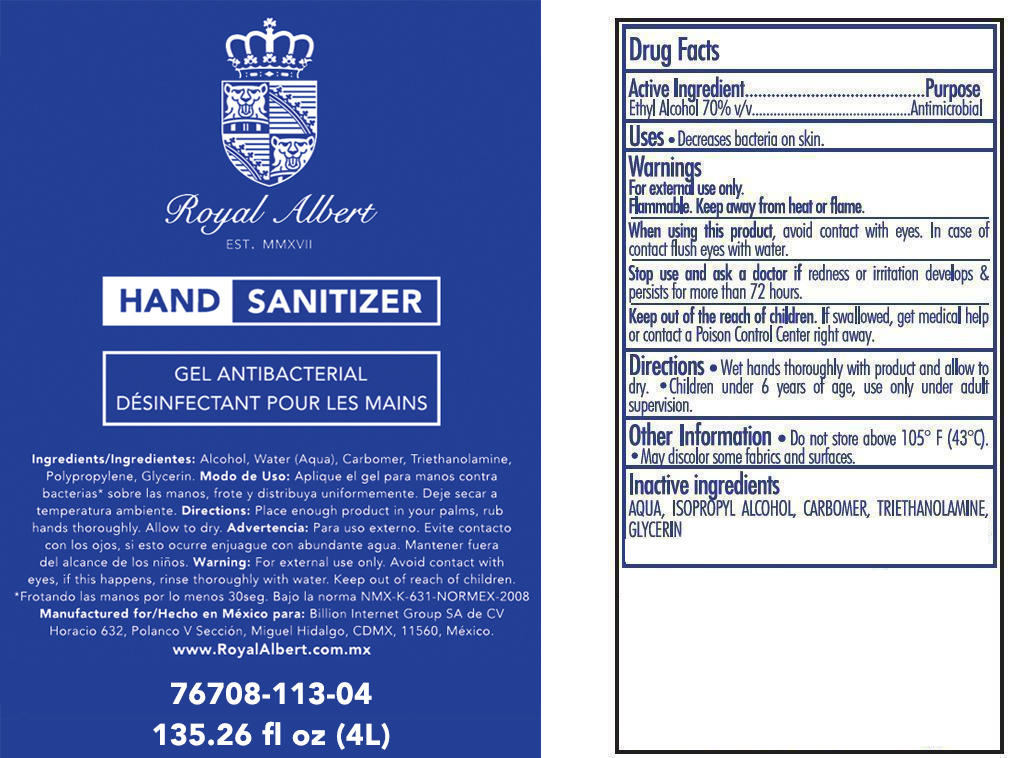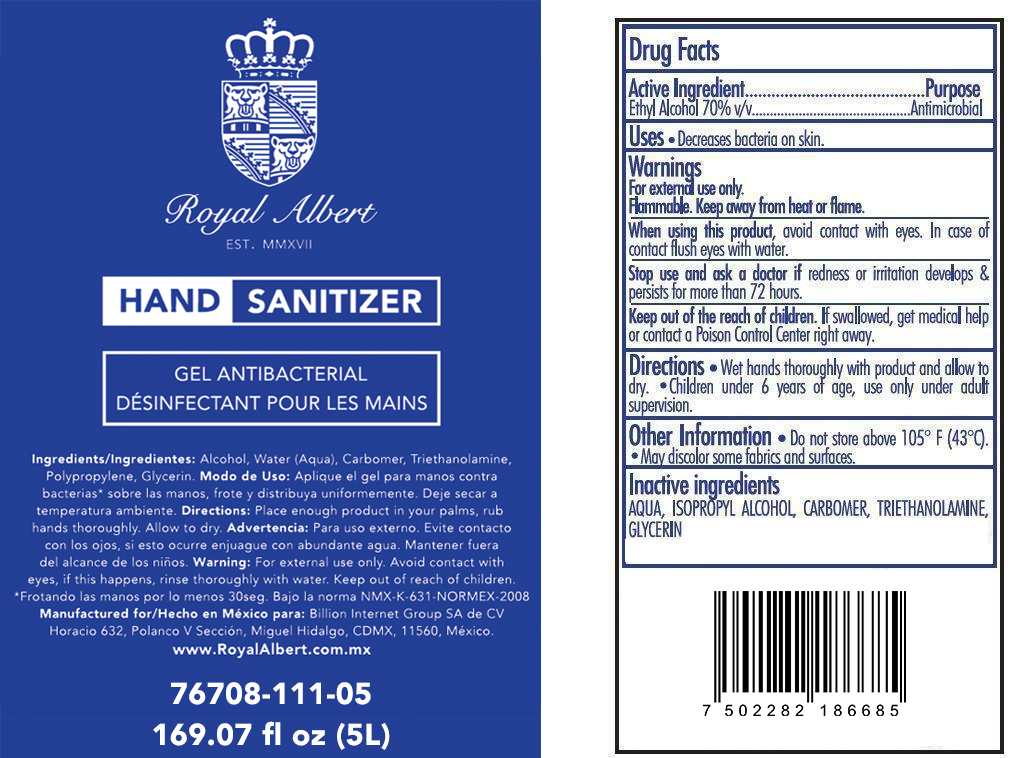 DRUG LABEL: Hand Sanitizer
NDC: 76708-112 | Form: GEL
Manufacturer: Billion Internet Group SA de CV
Category: otc | Type: HUMAN OTC DRUG LABEL
Date: 20200527

ACTIVE INGREDIENTS: ALCOHOL 175 mL/250 mL
INACTIVE INGREDIENTS: TROLAMINE; GLYCERIN; WATER; PROPYLENE GLYCOL; CARBOMER COPOLYMER TYPE A

This is a hand sanitizer manufactured according to the Temporary Policy for Preparation of Certain Alcohol-Based Hand Sanitizer Products During the Public Health Emergency (CoViD-19); Guidance for Industry.

The hand sanitizer is manufactured using only the following United States Pharmacopoeia (USP) grade ingredients in the preparation of the product (percentage in final product formulation) consistent with World Health Organization (WHO) recommendations:

1. Alcohol (ethanol) (USP or Food Chemical Codex (FCC) grade) (70%, volume/volume (v/v)) in an aqueous solution denatured according to Alcohol and Tobacco Tax and Trade Bureau regulations in 27 CFR part 20.
2. glycerin
3. triethanolamine
4. Carbomer
5. purified water USP

The firm does not add other active or inactive ingredients. Different or additional ingredients may impact the quality and potency of the product.

Active Ingredient(s)

Alcohol 70% v/v. Purpose: Antiseptic

Purpose

Antiseptic, Hand Sanitizer

Use

Decrease bacteria on skin

Warnings

For external use only. Flammable. Keep away from heat or flame

Do not use

Stop use and ask a doctor if redness or irritation
develops and persists for more than 72 hours.

When using this product, avoid contact with eyes.In
case of contact flush eyes with water.

Keep out of reach of children. If swallowed, get
medical help or contact a Poison Control Center right away.

Stop use and ask a doctor if redness or irritation
develops and persists for more than 72 hours.

Keep out of reach of children. If swallowed, get medical help or contact a Poison Control Center right away.

Directions

- Directions: Wet hands thoroughly with product, rub,
  and allow to dry. Children under 6 years of age, use only
  under adult supervision.

Other information

- Do not store above 105°F (43°C). May discolor some fabrics and surfaces.

Inactive ingredients

WATER (AQUA), CARBOMER, TRIETHANOLAMINE,
GLYCERIN.

Package Label - Principal Display Panel

5000 mL NDC: 76708-111-05

4000 mL NDC: 76708-113-04

20000 mL NDC: 76708-114-20

250 mL NDC: 76708-112-25